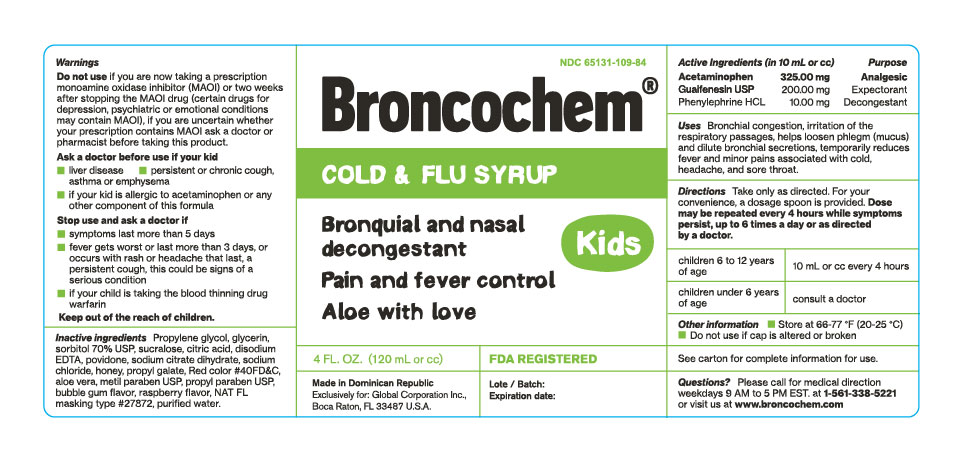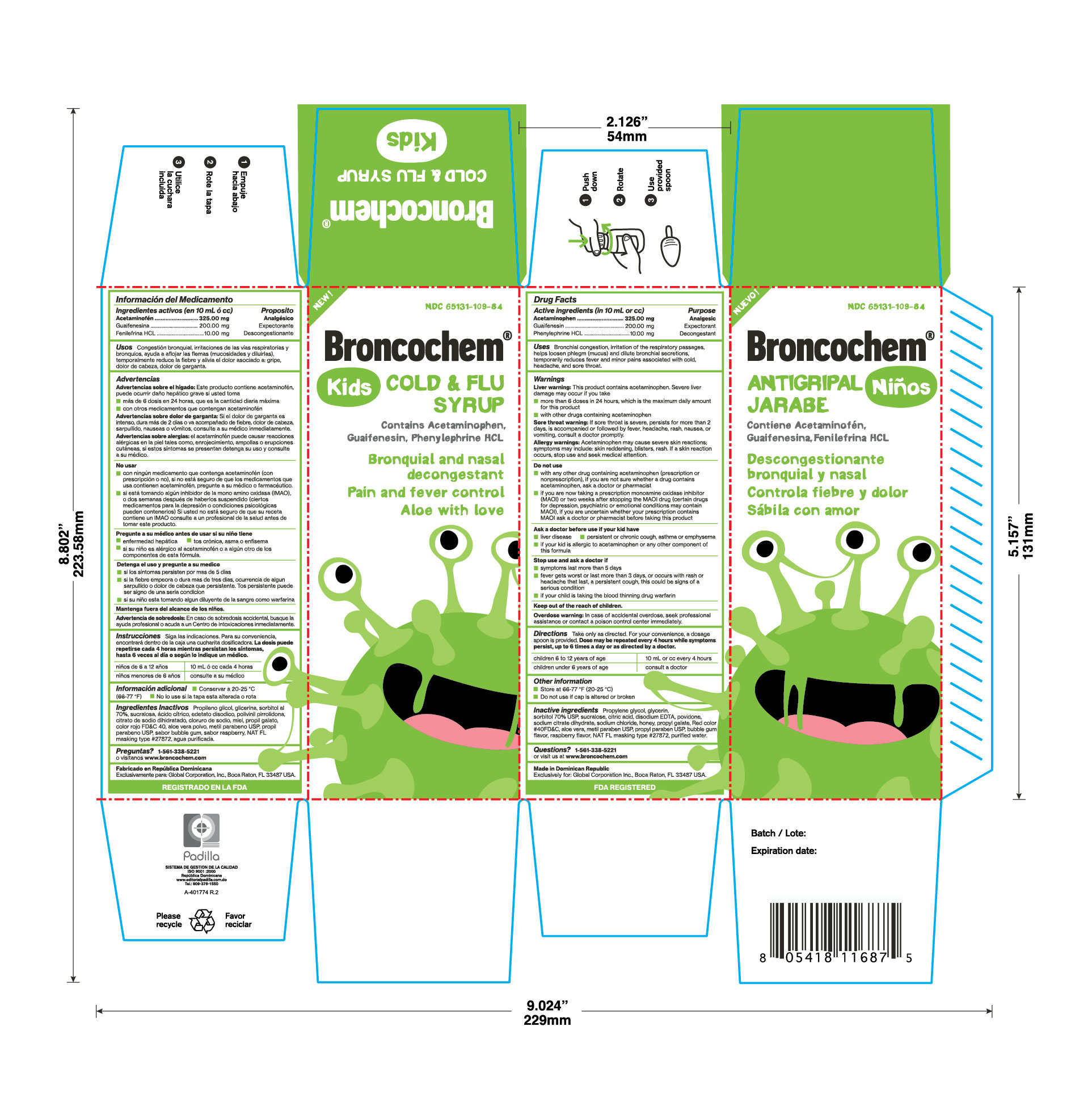 DRUG LABEL: BRONCOCHEM
NDC: 65131-109 | Form: SYRUP
Manufacturer: LABORATORIO MAGNACHEM INTERNATIONAL SRL
Category: otc | Type: HUMAN OTC DRUG LABEL
Date: 20250323

ACTIVE INGREDIENTS: ACETAMINOPHEN 325 mg/10 mL; PHENYLEPHRINE HYDROCHLORIDE 10 mg/10 mL; GUAIFENESIN 200 mg/10 mL
INACTIVE INGREDIENTS: PROPYLENE GLYCOL 1.5 mL/10 mL; GLYCERIN 2.5 mL/10 mL; SORBITOL 2 mL/10 mL; SUCRALOSE 15 mg/10 mL; CITRIC ACID MONOHYDRATE 20 mg/10 mL; DISODIUM HEDTA 0.9 mg/10 mL; POVIDONE K90 100 mg/10 mL; SODIUM CITRATE 40 mg/10 mL; SODIUM CHLORIDE 6.25 mg/10 mL; HONEY 100 mg/10 mL; PROPYL GALLATE 1 mg/10 mL; FD&C RED NO. 40 0.16 mg/10 mL; ALOE VERA LEAF 4 mg/10 mL; METHYLPARABEN 10 mg/10 mL; PROPYLPARABEN 1.5 mg/10 mL; RASPBERRY 0.0048 mL/10 mL; WATER 10 mL/10 mL

BRONCOCHEM KIDS COLD and FLU

Warnings

Liver warnings: this producto contains acetaminophen; severe liver damage may occur if you take:

More than 4 doses in 24 hour, wich is the maximum daily amount for this product.

With other drugs containing acetaminophen.

Sore throat warnings: if sore throat is severe, persist for more than 2 days, is accompanied or followed by fever, headache, rash, nauseas or vomiting, consult a doctor promptly.

allergy warnings: acetaminophen may cause severe skin reactions; symptoms may include:

Sking reddening, blisters, rash. If sking reactions occurs, stop use and seek medical attention.

Uses

Bronchial congestion, irritation of the respiratory passages, helps loosen phlegm (mucus) and dilute bronchial secretions, temporarily reduces fever and minor pains associated with cold, headache, and sore throat.

Active Ingredients

Acetaminophen...................325.00mg

Guaifenesin........................200.00mg

Phenylephrine HCl..................10.00mg

Ask a doctor before use if your kid have

Liver disease

Persistent or chronic cough, asthma or emphysema

If your kid is allergic to acetaminophen or any other componet of this formula

Stop use and ask a doctor if

Symtoms last more than 5 days

Fever gets worst or last more than 3 days, or occurs with rash or headache that last, a persistent cough, this could be signs of a serious conditions

If your child is taking the bloood thinning drug warfarin

Keep out of the reach of children

Overdose warning

In case of accidental overdose. seek professional assistance or contact a poison control center inmediately

Directions

Take only as directed, for your convenience a dosage spoon is provided. Do not exceed 6 doses in a 24 hour period

Children from 6 to 12 years-----10mL or cc every 4 hours

Children under 6 years, ask your doctor

Other information

store at 66-77*F (20-25*C), do not use if securety cap is altered or broken

Inactive ingredients

Propylene glycol, glycerin, Sorbitol USP, Sucralose, Citric acid, disodium Hedta, Povidone, Sodium citrate dihydrate, Sodium chloride, Honey, Propyl gallate, FD&C Red #40, Aloe Vera, Methylparaben USP, Propylparaben USP, Bubble Gum flavor, Raspberry flavor, Nat. Masking type #27872, Purified water.

Quiestions?

1-561-338-5221 or visit us at www.broncochem.com

Purose

Acetaminophen...........Analgesic

Guaifenesin................Expectorant

Phenylephrine.............Decongestant